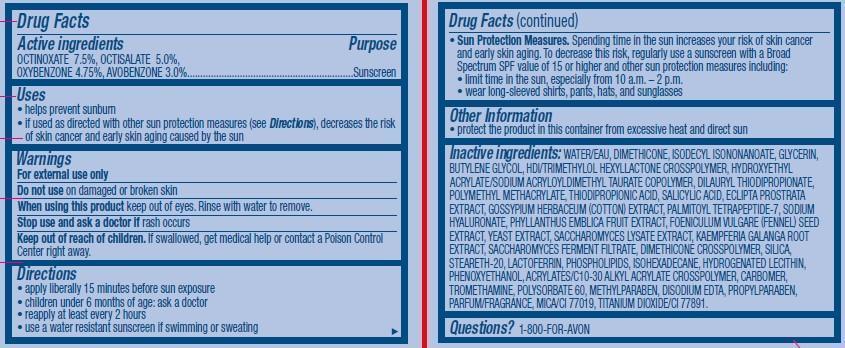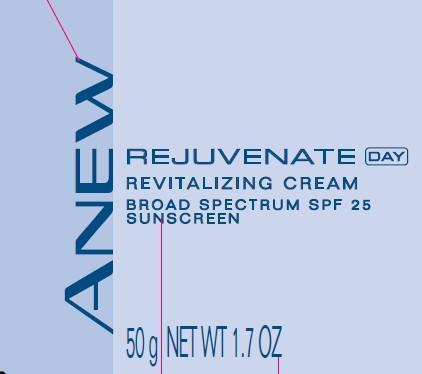 DRUG LABEL: Anew Rejuvenate
NDC: 10096-0305 | Form: CREAM
Manufacturer: Avon Products, Inc
Category: otc | Type: HUMAN OTC DRUG LABEL
Date: 20130530

ACTIVE INGREDIENTS: OCTINOXATE 75 mg/1 g; OCTISALATE 50 mg/1 g; OXYBENZONE 47.5 mg/1 g; AVOBENZONE 30 mg/1 g

Active ingredients
OCTINOXATE 7.5%, OCTISALATE 5.0%,
OXYBENZONE 4.75%, AVOBENZONE 3.0%...............................................................

Purpose
...................................Sunscreen

Uses

- helps prevent sunburn
- if used as directed with other sun protection measures (see Directions), decreases the risk of skin cancer and early skin aging caused by the sun

Warnings
For external use only

Do not use on damaged or broken skin

When using this product keep out of eyes. Rinse with water to remove.

Stop use and ask a doctor if rash occurs

Keep out of reach of children. If swallowed, get medical help or contact a Poison Control Center right away.

Directions

- apply liberally 15 minutes before sun exposure
- children under 6 months of age: ask a doctor
- reapply at least every 2 hours
- use a water resistant sunscreen if swimming or sweating
- Sun Protection Measures. Spending time in the sun increases your risk of skin cancer and early skin aging. To decrease this risk, regularly use a sunscreen with a Broad Spectrum SPF value of 15 or higher and other sun protection measures including:
- limit time in the sun, especially from 10 a.m. – 2 p.m.
- wear long-sleeved shirts, pants, hats, and sunglasses

Other Information

- protect the product in this container from excessive heat and direct sun

INACTIVE INGREDIENT

Inactive ingredients: WATER/EAU, DIMETHICONE, ISODECYL ISONONANOATE, GLYCERIN, BUTYLENE GLYCOL, HDI/TRIMETHYLOL HEXYLLACTONE CROSSPOLYMER, HYDROXYETHYL ACRYLATE/SODIUM ACRYLOYLDIMETHYL TAURATE COPOLYMER, DILAURYL THIODIPROPIONATE, POLYMETHYL METHACRYLATE, THIODIPROPIONIC ACID, SALICYLIC ACID, ECLIPTA PROSTRATA EXTRACT, GOSSYPIUM HERBACEUM (COTTON) EXTRACT, PALMITOYL TETRAPEPTIDE-7, SODIUM HYALURONATE, PHYLLANTHUS EMBLICA FRUIT EXTRACT, FOENICULUM VULGARE (FENNEL) SEED EXTRACT, YEAST EXTRACT, SACCHAROMYCES LYSATE EXTRACT, KAEMPFERIA GALANGA ROOT EXTRACT, SACCHAROMYCES FERMENT FILTRATE, DIMETHICONE CROSSPOLYMER, SILICA, STEARETH-20, LACTOFERRIN, PHOSPHOLIPIDS, ISOHEXADECANE, HYDROGENATED LECITHIN, PHENOXYETHANOL, ACRYLATES/C10-30 ALKYL ACRYLATE CROSSPOLYMER, CARBOMER, TROMETHAMINE, POLYSORBATE 60, METHYLPARABEN, DISODIUM EDTA, PROPYLPARABEN, PARFUM/FRAGRANCE, MICA/CI 77019, TITANIUM DIOXIDE/CI 77891.

Questions? 1-800-FOR-AVON